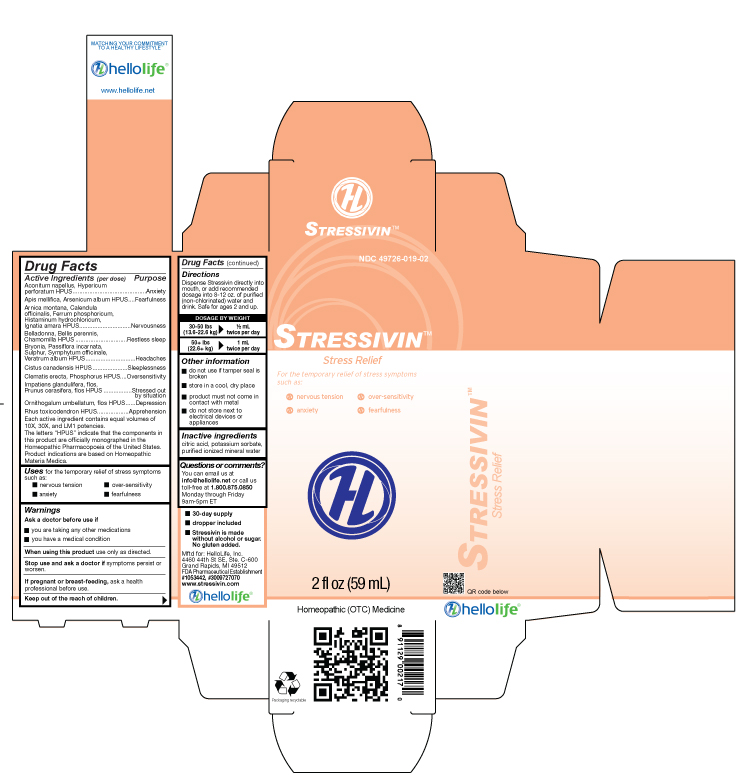 DRUG LABEL: Stressivin
NDC: 49726-019 | Form: LIQUID
Manufacturer: Hello Life, Inc.
Category: homeopathic | Type: HUMAN OTC DRUG LABEL
Date: 20181226

ACTIVE INGREDIENTS: ACONITUM NAPELLUS 10 [hp_X]/59 mL; APIS MELLIFERA 10 [hp_X]/59 mL; ARNICA MONTANA 10 [hp_X]/59 mL; ARSENIC TRIOXIDE 10 [hp_X]/59 mL; ATROPA BELLADONNA 10 [hp_X]/59 mL; BELLIS PERENNIS 10 [hp_X]/59 mL; BRYONIA ALBA ROOT 10 [hp_X]/59 mL; CALENDULA OFFICINALIS FLOWERING TOP 10 [hp_X]/59 mL; MATRICARIA RECUTITA 10 [hp_X]/59 mL; HELIANTHEMUM CANADENSE 10 [hp_X]/59 mL; CLEMATIS RECTA FLOWERING TOP 10 [hp_X]/59 mL; FERRUM PHOSPHORICUM 10 [hp_X]/59 mL; HISTAMINE DIHYDROCHLORIDE 10 [hp_X]/59 mL; HYPERICUM PERFORATUM 10 [hp_X]/59 mL; STRYCHNOS IGNATII SEED 10 [hp_X]/59 mL; IMPATIENS GLANDULIFERA FLOWER 10 [hp_X]/59 mL; ORNITHOGALUM UMBELLATUM 10 [hp_X]/59 mL; PASSIFLORA INCARNATA FLOWER 10 [hp_X]/59 mL; PHOSPHORUS 10 [hp_X]/59 mL; PRUNUS CERASIFERA FLOWER 10 [hp_X]/59 mL; TOXICODENDRON PUBESCENS LEAF 10 [hp_X]/59 mL; SULFUR 10 [hp_X]/59 mL; COMFREY ROOT 10 [hp_X]/59 mL; VERATRUM ALBUM ROOT 10 [hp_X]/59 mL
INACTIVE INGREDIENTS: WATER; CITRIC ACID MONOHYDRATE; POTASSIUM SORBATE

Drug Facts

Active Ingredients (per dose)

Aconitum napellus, Hypericum perforatum HPUS
Apis mellifica, Arsenicum album HPUS
Arnica montana, Calendula
officinalis, Ferrum phosphoricum,
Histaminum hydrochloricum,
Ignatia amara HPUS
Belladonna, Bellis perennis,
Chamomilla HPUS
Bryonia, Passiflora incarnata,
Sulphur, Symphytum officinale,
Veratrum album HPUS
Cistus canadensis HPUS
Clematis erecta, Phosphorus HPUS
Impatiens glandulifera, flos,
Prunus cerasifera, flos HPUS
Ornithogalum umbellatum, flos HPUS
Rhus toxicodendron HPUS
Each active ingredient contains equal volumes of 10X, 30X and LM1 potencies.
The letters “HPUS” indicate that the components in this product are officially monographed in the Homeopathic Pharmacopoeia of the United States.
Product indications are based on Homeopathic Materia Medica.

Purpose

Aconitum napellus, Hypericum
perforatum HPUS….......................................Anxiety
Apis mellifica, Arsenicum album HPUS.....Fearfulness
Arnica montana, Calendula
officinalis, Ferrum phosphoricum,
Histaminum hydrochloricum,
Ignatia amara HPUS…...........................Nervousness
Belladonna, Bellis perennis,
Chamomilla HPUS.............................Restless Sleep
Bryonia, Passiflora incarnata,
Sulphur, Symphytum officinale,
Veratrum album HPUS............................Headaches
Cistus canadensis HPUS.......................Sleeplessness
Clematis erecta, Phosphorus HPUS....Oversensitivity
Impatiens glandulifera, flos,
Prunus cerasifera, flos HPUS..........Stressed out by situation
Ornithogalum umbellatum, flos HPUS.....Depression
Rhus toxicodendron HPUS………….…….Apprehension

Uses

to temporarily relieve symptoms commonly associated with stress such as:
• nervous tension
• over-sensitivity
• anxiety
• fearfulness

Warnings

Ask a doctor before use if

• you are taking any other medications
• you have a medical condition

When using this product

use only as directed.

Stop use and ask a doctor if

symptoms persist or worsen.

If pregnant or breast-feeding,

ask a health professional before use.

Keep out of the reach of children.

Directions

Dispense Stressivin directly into mouth, or add recommended dosage into 8-12 oz. of purified (non-chlorinated) water and drink. Safe for ages 2 and up.

DOSAGE BY WEIGHT

30-50 lbs 1/2 mL
(13.6-22.6 kg) twice per day
50+ lbs 1 mL
(22.6+ kg) twice per day

Other information

• do not use if tamper seal is broken
• store in a cool, dry place
• product must not come in contact with metal
• do not store next to electrical devices or appliances

Inactive ingredients

citric acid, potassium sorbate, purified ionized mineral water

Questions or comments?

You can email us at info@hellolife.net or call us toll-free at
1.800.875.0850. Monday through Friday, 9am-5pm ET

DESCRIPTION

- 30-day supply
- dropper included
- Stressivin is made without alcohol or sugar. No gluten added.

Mftd for: HelloLife, LLC
4460 44th St SE, Ste. C-600
Grand Rapids, MI 49512
FDA Pharmaceutical Establishment
#1053442, #3009727070
www.stressivin.com

Principal Display Panel

NDC 49726-019-02

StressivinTM

Stress Relief

To temporarily relieve symptoms commonly associated with stress such as:

• nervous tension
• over-sensitivity
• anxiety
• fearfulness
2 fl oz (59 mL)
Homeopathic (OTC) Medicine